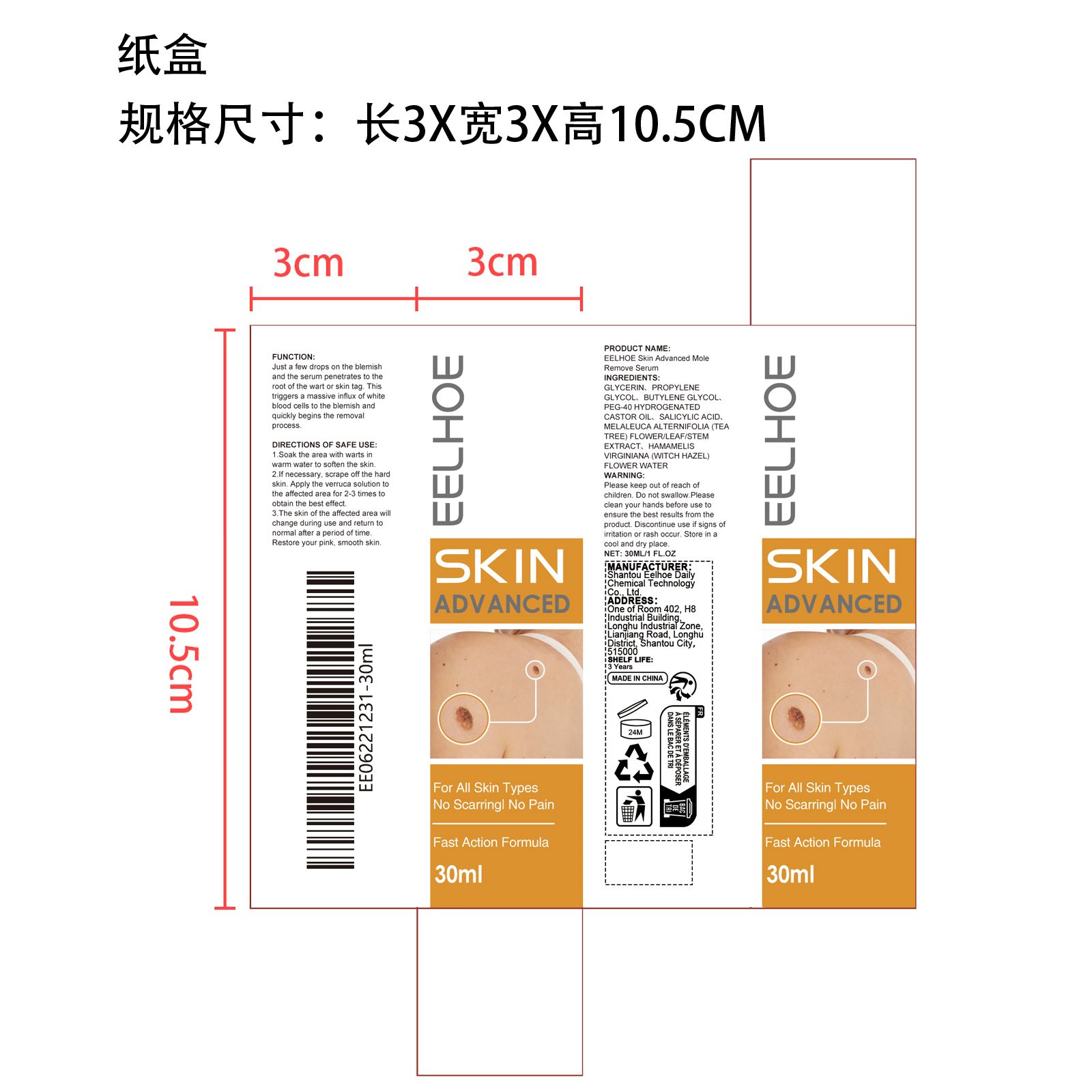 DRUG LABEL: EELHOE Skin Advanced Mole Remove Serum
NDC: 85064-012 | Form: LIQUID
Manufacturer: Shantou Eelhoe Daily Chemical Technology Co., Ltd.
Category: otc | Type: HUMAN OTC DRUG LABEL
Date: 20251127

ACTIVE INGREDIENTS: MELALEUCA ALTERNIFOLIA FLOWERING TOP 0.006 mg/30 mg; HAMAMELIS VIRGINIANA (WITCH HAZEL) LEAF WATER 0.006 mg/30 mg
INACTIVE INGREDIENTS: BUTYLENE GLYCOL 9 mg/30 mg; SALICYLIC ACID 0.006 mg/30 mg; PEG-40 HYDROGENATED CASTOR OIL 0.03 mg/30 mg; PROPYLENE GLYCOL 9 mg/30 mg; GLYCERIN 11.952 mg/30 mg

ACTIVE INGREDIENT

MELALEUCA ALTERNIFOLIA FLOWERING TOP、HAMAMELIS VIRGINIANA (WITCH HAZEL) LEAF WATER

WHEN USING

1: Soak the area with warts in warm water to soften the skin

2: If necessary, scrape off the hard skin. Apply the verruca solution to the affected area for 2-3 times to obtain the best effect.

3: The skin of the affected area will change during use and return to normal after a period of time.Restore your pink, smooth skin

PURPOSE

Just a few drops on the blemish and the serum penetrates to the roct of the wart or skin tag. This triggers a massive influx of white blood cells to the blemish and quickly begins the removal process.

WARNINGS

Please keep out of reach of children. Do not swallow.Please clean your hands before use to ensure the best results from the product. Discontinue use if signs of irritation or rash occur. Store in a cool and dry place.

DO NOT USE

Discontinue use if signs of irritation or rash occur.

STOP USE

Discontinue use if signs of irritation or rash occur.

KEEP OUT OF REACH OF CHILDREN

Please keep out of reach of children. Do not swallow.

STORAGE AND HANDLING

Store in a cool and dry place.

INACTIVE INGREDIENT

GLYCERIN、PROPYLENE GLYCOL、BUTYLENE GLYCOL、PEG-40 HYDROGENATED CASTOR OIL、SALICYLIC ACID

DOSAGE AND ADMINISTRATION

1: Soak the area with warts in warm water to soften the skin

2: If necessary, scrape off the hard skin. Apply the verruca solution to the affected area for 2-3 times to obtain the best effect.

INDICATIONS AND USAGE

1: Soak the area with warts in warm water to soften the skin

2: If necessary, scrape off the hard skin. Apply the verruca solution to the affected area for 2-3 times to obtain the best effect.

3: The skin of the affected area will change during use and return to normal after a period of time.Restore your pink, smooth skin